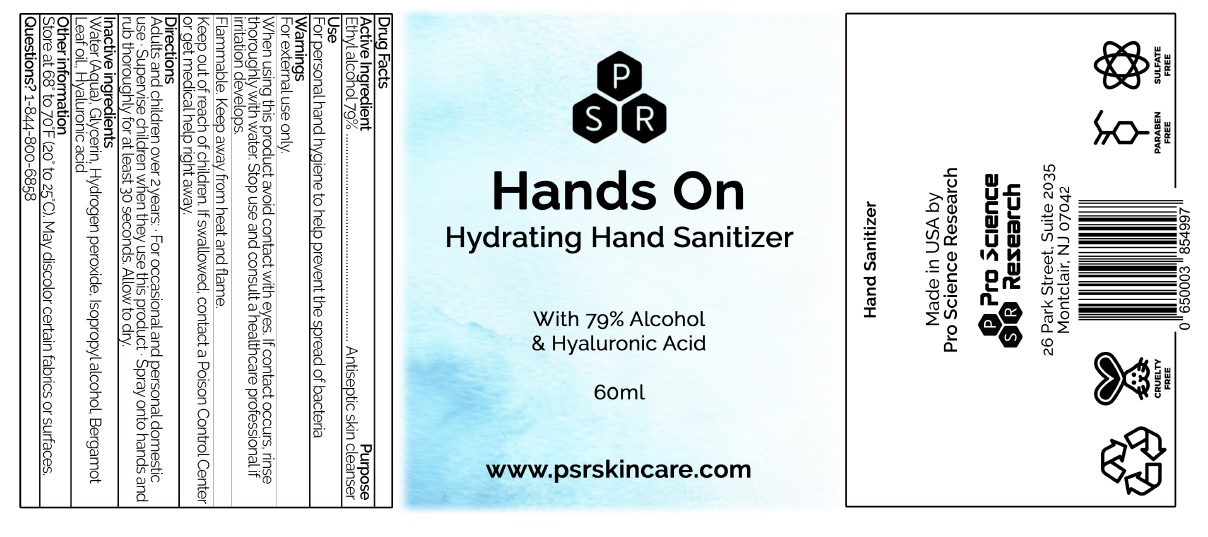 DRUG LABEL: Hands on Hydrating Hand Sanitizer
NDC: 75306-001 | Form: LIQUID
Manufacturer: D-Time Limited Liability Company
Category: otc | Type: HUMAN OTC DRUG LABEL
Date: 20211101

ACTIVE INGREDIENTS: ALCOHOL 79 mL/100 mL
INACTIVE INGREDIENTS: GLYCERIN; HYDROGEN PEROXIDE; WATER; ISOPROPYL ALCOHOL; BERGAMOT OIL; HYALURONIC ACID

Active Ingredient

Alcohol 79% v/v.

Purpose

Antiseptic skin cleanser

Use

For personal hand hygiene to help prevent the spread of bacteria

Warning

For external use only
When using this product avoid contact with eyes.
Flammable. Keep away from heat and flame.

Ask doctor

Stop use and consult a healthcare professional if irritation develops.

Keep out of reach of children.

If swallowed, contact a Poison Control Center or , get medical help right away.

Directions

Adults and children over 2 years: ∙ For occasional and personal domestic use ∙ Supervise children when they use this product ∙ Spray onto hands and rub thoroughly for at least 30 seconds. Allow to dry.

Inactive ingredients

Water (Aqua), Glycerin, Hydrogen peroxide, Isopropyl alcohol, Bergamot leaf oil, Hyaluronic acid

Other information

Store at 68 to 70 F (20 to 25 C). May discolor certain fabrics on surfaces

Questions?

1-844-800-6858